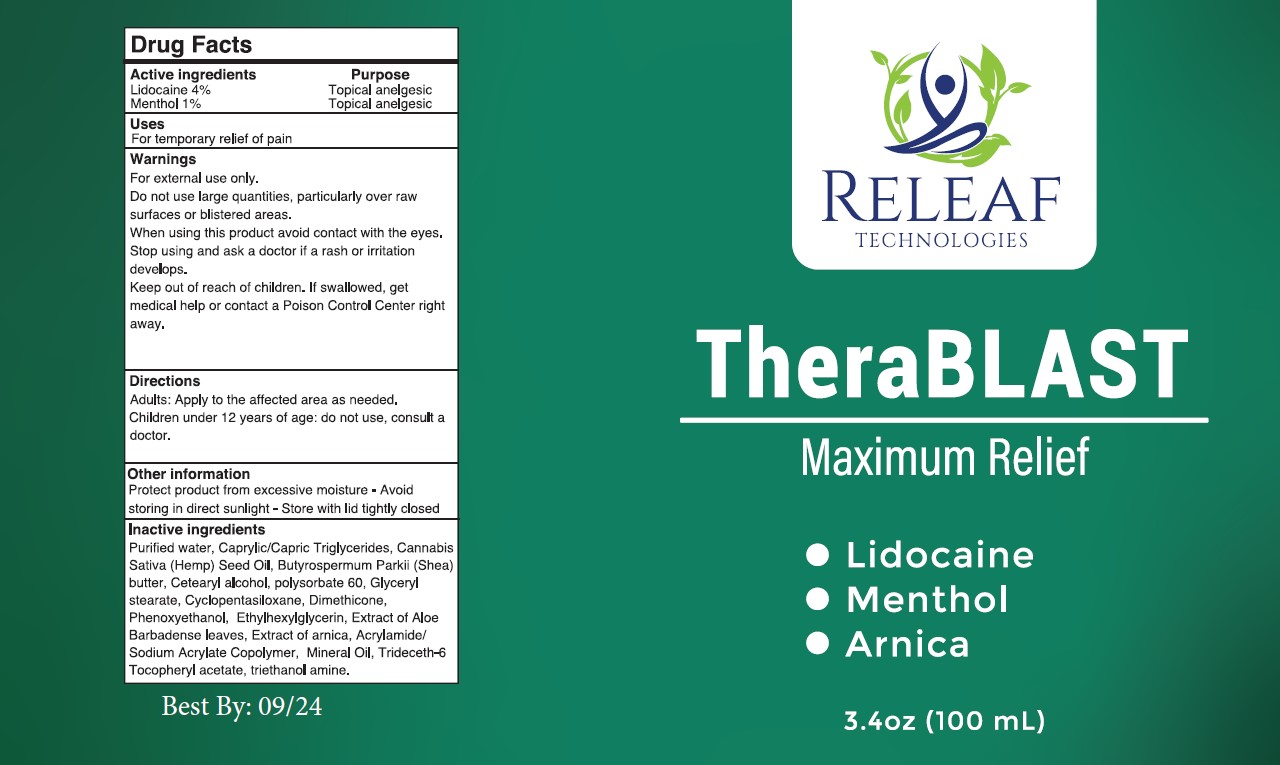 DRUG LABEL: THERABLAST
NDC: 78663-201 | Form: LOTION
Manufacturer: Releaf Technologies LLC
Category: otc | Type: HUMAN OTC DRUG LABEL
Date: 20250108

ACTIVE INGREDIENTS: LIDOCAINE 4 g/100 mL; MENTHOL 1 g/100 mL
INACTIVE INGREDIENTS: TROLAMINE; TRIDECETH-6; ALPHA-TOCOPHEROL ACETATE; MEDIUM-CHAIN TRIGLYCERIDES; WATER; HEMP; SHEA BUTTER; CETOSTEARYL ALCOHOL; POLYSORBATE 60; GLYCERYL MONOSTEARATE; DIMETHICONE; PHENOXYETHANOL; ETHYLHEXYLGLYCERIN; ALOE VERA LEAF; ARNICA MONTANA; ACRYLIC ACID/SODIUM ACRYLATE COPOLYMER (1:1; 600 MPA.S AT 0.2%); MINERAL OIL; CYCLOMETHICONE 5

RELEAF TECHNOLOGIES (as PLD) - THERABLAST (78663-201)

ACTIVE INGREDIENT

Lidocaine 4%
Menthol 1%

PURPOSE

TOPICAL ANALGESIC

USES

For temporary relief of pain

WARNING

For external use only.

Do not use large quantities, particularly over raw surfaces or blistered areas.

When using this product avoid contact with the eyes.

Stop using and ask a doctor if

- the condition worsens
- symptoms persist for more than 7 days
- symptoms clear up and occur again within a few days
- a rash or irritation develops.

Keep out of reach of children. If swallowed, get medical help or contact a Poison Control Center right away.

DIRECTIONS

Adults and children 12 years of age and older: apply to the affected area not more than 3 to 4 times daily.
Children under 12 years of age: do not use, ask a doctor.

OTHER INFORMATION

Protect product from excessive moisture - Avoid storing in direct sunlight - Store with lid tightly closed

INACTIVE INGREDIENTS

Purified water, Caprylic/Capric Triglycerides, Butyrospermum Parkii (Shea) butter, Cetearyl alcohol, polysorbate 60, Glyceryl stearate, Cyclopentasiloxane, Dimethicone, Phenoxyethanol, Ethylhexylglycerin, me, Extract of Aloe Barbadense leaves, Extract of arnica,
Acrylamide/Sodium Acrylate Copolymer, Mineral Oil, Trideceth-6 Tocopheryl acetate, triethanol amine.